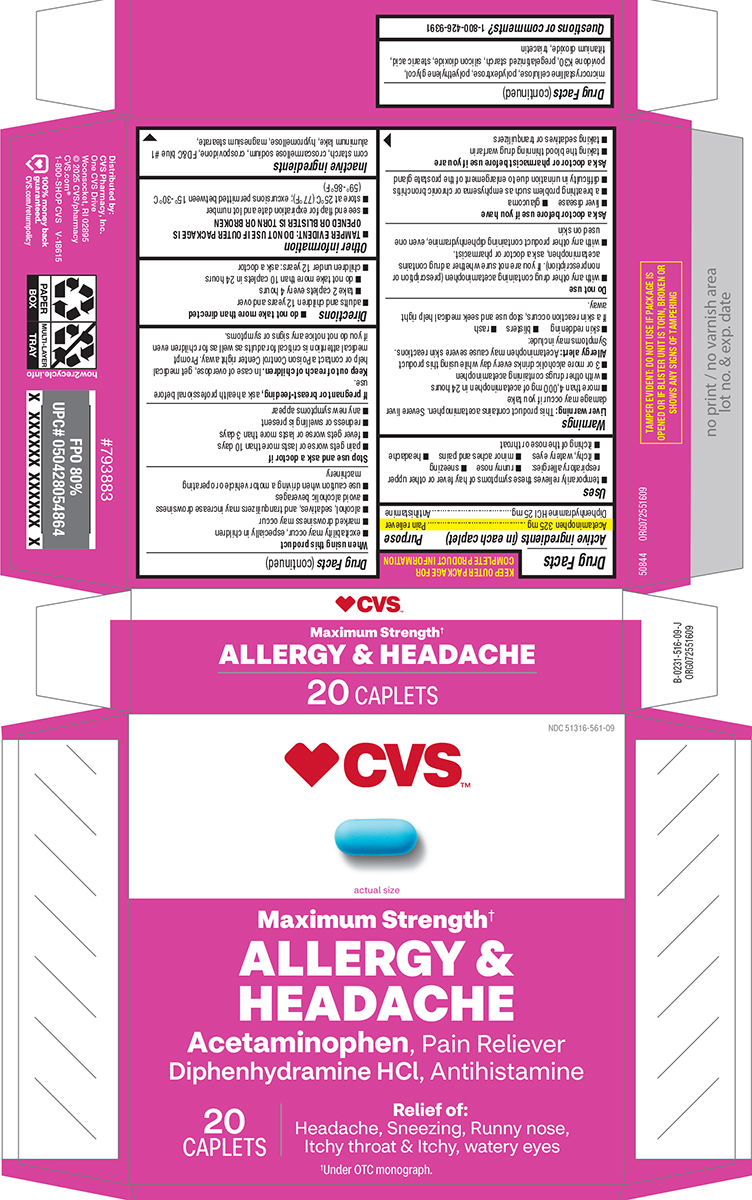 DRUG LABEL: Allergy and Headache
NDC: 51316-561 | Form: TABLET, FILM COATED
Manufacturer: CVS WOONSOCKET PRESCRIPTION CENTER, INCORPORATED
Category: otc | Type: HUMAN OTC DRUG LABEL
Date: 20251107

ACTIVE INGREDIENTS: ACETAMINOPHEN 325 mg/1 1; DIPHENHYDRAMINE HYDROCHLORIDE 25 mg/1 1
INACTIVE INGREDIENTS: STARCH, CORN; CROSCARMELLOSE SODIUM; CROSPOVIDONE, UNSPECIFIED; FD&C BLUE NO. 1 ALUMINUM LAKE; HYPROMELLOSE, UNSPECIFIED; MAGNESIUM STEARATE; MICROCRYSTALLINE CELLULOSE; POLYDEXTROSE; POLYETHYLENE GLYCOL, UNSPECIFIED; POVIDONE K30; SILICON DIOXIDE; STEARIC ACID; TITANIUM DIOXIDE; TRIACETIN

CVS 44-516

Active ingredients (in each caplet)

Acetaminophen 325 mg
Diphenhydramine HCl 25 mg

Purpose

Pain reliever
Antihistamine

Uses

- temporarily relieves these symptoms of hay fever or other upper respiratory allergies
  - runny nose
  - sneezing
  - itchy, watery eyes
  - minor aches and pains
  - headache
  - itching of the nose or throat

Warnings

Liver warning: This product contains acetaminophen. Severe liver damage may occur if you take

- more than 4,000 mg of acetaminophen in 24 hours
- with other drugs containing acetaminophen
- 3 or more alcoholic drinks every day while using this product

Allergy alert: Acetaminophen may cause severe skin reactions. Symptoms may include:

- skin reddening
- blisters
- rash

If a skin reaction occurs, stop use and seek medical help right away.

Do not use

- with any other drug containing acetaminophen (prescription or nonprescription). If you are not sure whether a drug contains acetaminophen, ask a doctor or pharmacist.
- with any other product containing diphenhydramine, even one used on skin

Ask a doctor before use if you have

- liver disease
- glaucoma
- a breathing problem such as emphysema or chronic bronchitis
- difficulty in urination due to enlargement of the prostate gland

Ask a doctor or pharmacist before use if you are

- taking the blood thinning drug warfarin
- taking sedatives or tranquilizers

When using this product

- excitability may occur, especially in children
- marked drowsiness may occur
- alcohol, sedatives, and tranquilizers may increase drowsiness
- avoid alcoholic beverages
- use caution when driving a motor vehicle or operating machinery

Stop use and ask a doctor if

- pain gets worse or lasts more than 10 days
- fever gets worse or lasts more than 3 days
- redness or swelling is present
- any new symptoms appear

If pregnant or breast-feeding,

ask a health professional before use.

Keep out of reach of children.

In case of overdose, get medical help or contact a Poison Control Center right away. Prompt medical attention is critical for adults as well as for children even if you do not notice any signs or symptoms.

Directions

- do not take more than directed
- adults and children 12 years and over
  - take 2 caplets every 4 hours
  - do not take more than 10 caplets in 24 hours
- children under 12 years: ask a doctor

Other information

- TAMPER EVIDENT: DO NOT USE IF OUTER PACKAGE IS OPENED OR BLISTER IS TORN OR BROKEN
- see end flap for expiration date and lot number
- store at 25°C (77°F); excursions permitted between 15°-30°C (59°-86°F)

Inactive ingredients

corn starch, croscarmellose sodium, crospovidone, FD&C blue #1 aluminum lake, hypromellose, magnesium stearate, microcrystalline cellulose, polydextrose, polyethylene glycol,
povidone K30, pregelatinized starch, silicon dioxide, stearic acid, titanium dioxide, triacetin

Questions or comments?

1-800-426-9391

Principal display panel

♥︎CVS™

NDC 51316-561-09

actual size

Maximum Strength†
ALLERGY &
HEADACHE

Acetaminophen, Pain Reliever
Diphenhydramine HCl, Antihistamine

20
CAPLETS

Relief of:
Headache, Sneezing, Runny nose,
Itchy throat & Itchy, watery eyes

†Under OTC monograph.

TAMPER EVIDENT: DO NOT USE IF PACKAGE IS
OPENED OR IF BLISTER UNIT IS TORN, BROKEN OR
SHOWS ANY SIGNS OF TAMPERING

50844 ORG072551609

Distributed by:
CVS Pharmacy, Inc.
One CVS Drive
Woonsocket, RI 02895
© 2025 CVS/pharmacy
CVS.com®
1-800-SHOP CVS V-18615

100% money back
guaranteed.
CVS.com/returnpolicy

CVS 44-516